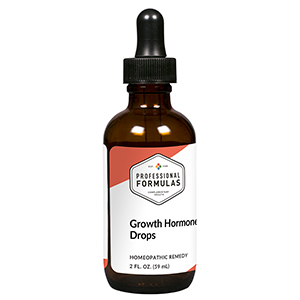 DRUG LABEL: Growth Hormone Drops
NDC: 63083-2160 | Form: LIQUID
Manufacturer: Professional Complementary Health Formulas
Category: homeopathic | Type: HUMAN OTC DRUG LABEL
Date: 20190815

ACTIVE INGREDIENTS: ACETYLCARNITINE 3 [hp_X]/59 mL; ARGININE 3 [hp_X]/59 mL; LYSINE 3 [hp_X]/59 mL; ORNITHINE 3 [hp_X]/59 mL; CORTICOTROPIN 6 [hp_X]/59 mL; SUS SCROFA ADRENAL GLAND 6 [hp_X]/59 mL; CREATINE MONOHYDRATE 6 [hp_X]/59 mL; CERVUS ELAPHUS HORN 6 [hp_X]/59 mL; .GAMMA.-AMINOBUTYRIC ACID 6 [hp_X]/59 mL; GLUTAMINE 6 [hp_X]/59 mL; BOS TAURUS HYPOTHALAMUS 6 [hp_X]/59 mL; DALOTUZUMAB 12 [hp_X]/59 mL; PHOSPHATIDYL SERINE 6 [hp_X]/59 mL; BOS TAURUS PITUITARY GLAND, POSTERIOR 6 [hp_X]/59 mL; TRYPTOPHAN 6 [hp_X]/59 mL; SOMATROPIN 6 [hp_X]/59 mL; UBIDECARENONE 8 [hp_X]/59 mL
INACTIVE INGREDIENTS: ALCOHOL; WATER

C160

ACTIVE INGREDIENTS

Acetyl L-Carnitine 3X
Arginine 3X
Lysine 3X
OKG 3X
ACTH 6X
Adrenal cortex 6X
Creatine monohydrate 6X
Deer antler 6X
GABA 6X
Glutamine 6X
Hypothalamus 6X
IGF-1 12X
Phosphatidylserine 6X
Pituitary 6X
Tryptophan 6X
Growth hormone 6X, 12X
Coenzyme Q10 8X

QUESTIONS

Professional Formulas

PO Box 2034 Lake Oswego, OR 97035

INDICATIONS

For the temporary relief of feeling tired, listless, easily fatigued, or experiencing reduced strength, difficulty concentrating, or a lack of motivation.*

PURPOSE

*Claims based on traditional homeopathic practice, not accepted medical evidence. Not FDA evaluated.

WARNINGS

In case of overdose, get medical help or contact a poison control center right away.

Keep out of the reach of children.

PREGNANCY OR BREAST FEEDING

If pregnant or breastfeeding, ask a healthcare professional before use.

DIRECTIONS

Place drops under tongue 30 minutes before/after meals. Adults and children 12 years and over: Take 10 drops up to 3 times per day. Consult a physician for use in children under 12 years of age. Not intended for use in infants.

OTHER INFORMATION

Tamper resistant. If seal is broken, do not use. After opening, close container tightly and store at room temperature away from heat.

INACTIVE INGREDIENTS

20% ethanol, purified water.

LABEL

Est 1985

Professional Formulas

Complementary Health

Growth Hormone Drops

Homeopathic Remedy

2 FL. OZ. (59 mL)